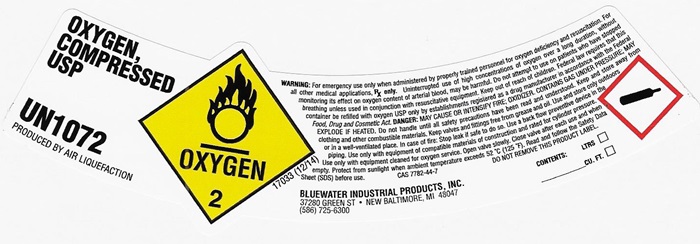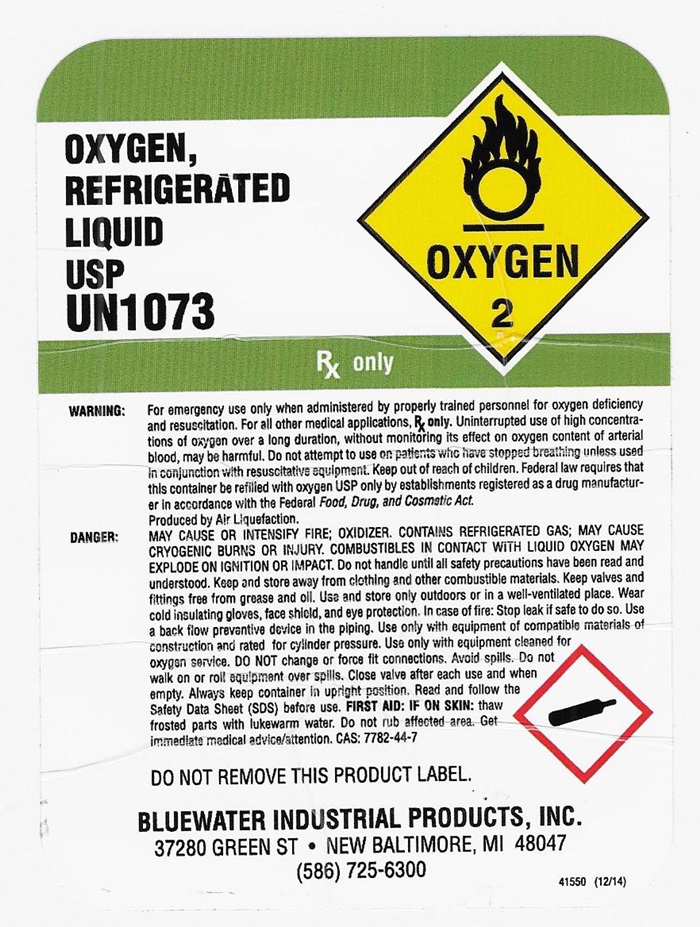 DRUG LABEL: OXYGEN
NDC: 44517-001 | Form: GAS
Manufacturer: Corrigan Propane LLC dba Blue Water Industrial Products
Category: prescription | Type: HUMAN PRESCRIPTION DRUG LABEL
Date: 20260125

ACTIVE INGREDIENTS: OXYGEN 99 L/100 L

OXYGEN COMPRESSED LABEL

OXYGEN, COMPRESSED USP UN 1072 OXYGEN 217033 (12/14)

PRODUCED BY AIR LIQUEFACTION

WARNING:For emergency use only when administered by properly trained personnel for oxygen deficiency and resuscitation. For all other medical applications, Rx only. Uninterrupted use of high concentrations of oxygen over a long duration, without monitoring its effect on oxygen content of arterial blood, may be harmful. Do not attempt to use on patients who have stopped breathing unless used in conjunction with resuscitative equipment. DANGER:MAY CAUSE OR INTENSIFY FIRE; OXIDIZER. CONTAINS GAS UNDER PRESSURE; MAY EXPLODE IF HEATED. Do not handle until all safety precautions have been read and understood. Keep and store away from clothing and other combustible materials. Keep valves and fittings free from grease and oil. Use and store only outdoors or in a well-ventilated place. In case of fire: Stop leak if safe to do so. Use a back flow preventive device in the piping. Use only with equipment of compatible materials of construction and rated for cylinder pressure. Use only with equipment cleaned for oxygen service. Open valve slowly. Close valve after each use and when empty. Protect from sunlight when ambient temperature exceeds 52°C (125° F). Read and follow the Safety Data Sheet (SDS) before use. CAS 7782-44-7 DO NOT REMOVE THIS PRODUCT LABEL.

CONTENTS:

LTRS: ___

CU.FT. ___

BLUEWATER INDUSTRIAL PRODUCTS INC.

37280 GREEN ST • NEW BALTIMORE, MI 48047

(586) 725-6300

Refrigerated Liquid Oxygen Label

OXYGEN, REFRIERATED LIQUID USP UN1073

Rx ONLY

Rx ONLY.

WARNING:For emergency use only when administered by properly trained personnel for oxygen deficiency and resuscitation. For all other medical applications, Rx only. Uninterrupted use of high concentrations of oxygen over a long duration, without monitoring its effect on oxygen content of arterial blood, may be harmful. Do not attempt to use on patients who have stopped breathing unless used in conjunction of resuscitative equipment. Produced by Air Liquefaction.

DANGER:MAY CAUSE OR INTENSIFY FIRE; OXIDER, CONTAINS REFRIGERATED GAS; MAY CAUSE CRYOGENIC BURNS OR INJURY. COMBUSTIBELS IN CONTACT WITH LIQUID OXYGEN MAY EXPLODE ON IGNITION OR IMPACT. Do not handle until all safety precautions have been read and understood. Keep and store away from clothing and other combustible materials. Keep valves and fittings free from grease and oil. Use and store only outdoors or in a well-ventilated place. Wear cold insulating gloves, face shield, and eye protection. In case of fire: Stop leak if safe to do so. Use a back flow preventive device in the piping. Use only the equipment of compatible materials equipment cleaned for oxygen service. DO NOT change or force fit connections. Avoid spills. Do not walk on or roll equipment over spills. Close valve after each use and when empty. Always keep container in upright position. Read and follow the Safety Data Sheet (SDS) before use. FIRST AID FIRST AID: IF ON SKIN: Thaw affected parts with lukewarm water. Do not rub affected area. Get immediate medical advice/attention. CAS: 7782-44-7

DO NOT REMOVE THIS PRODUCT LABEL

BLUEWATER INDUSTRIAL PRODUCTS INC.

37280 GREEN ST • NEW BALTIMORE, MI 48047

(586) 725-6300

41550 (12/14)